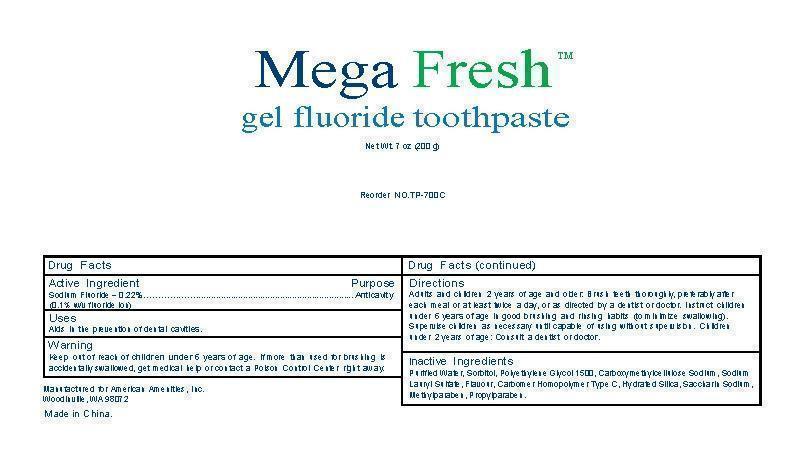 DRUG LABEL: MegaFresh
NDC: 54157-102 | Form: GEL, DENTIFRICE
Manufacturer: American Amenities, Inc.
Category: otc | Type: HUMAN OTC DRUG LABEL
Date: 20150116

ACTIVE INGREDIENTS: SODIUM FLUORIDE 0.10 g/100 g
INACTIVE INGREDIENTS: WATER; SORBITOL; POLYETHYLENE GLYCOL 1500; CARBOXYMETHYLCELLULOSE SODIUM; SODIUM LAURYL SULFATE; CARBOMER HOMOPOLYMER TYPE C; HYDRATED SILICA; SACCHARIN SODIUM; METHYLPARABEN; PROPYLPARABEN

Active Ingredient: Sodium Fluoride (0.22%)

Purpose: Anticavity

INDICATIONS AND USAGE

Uses: Aids in the prevention of dental cavities

WARNINGS

For external use only. Keep out of reach of children

Keep out of reach of children under six years of age

ASK DOCTOR

If more than used for brushing is accidentally swallowed, get medical help or contact a poison control center immediately.

DOSAGE AND ADMINISTRATION

Adults and children of two years of age and older: Brush teeth thoroughly, perferrably after each meal or at least twice a day, or as directed by a dentist or a doctor. Instruct children under six years of age in good brushing and rinsing habit (to minimize swollowing). Supervise children as necessary until capable of using without supervision. Children under 2 years of age: consult a dentist or doctor.

INACTIVE INGREDIENT

Purified Water,Sorbitol, Polyethylene Glycol 1500, Carboxymethylcellulose Sodium, Sodium Lauryl Sulfate, Flavour, Carbomer Homopolymer Type C, Hydrated Silica, Saccharin Sodium,Methylparaben, Propylparaben